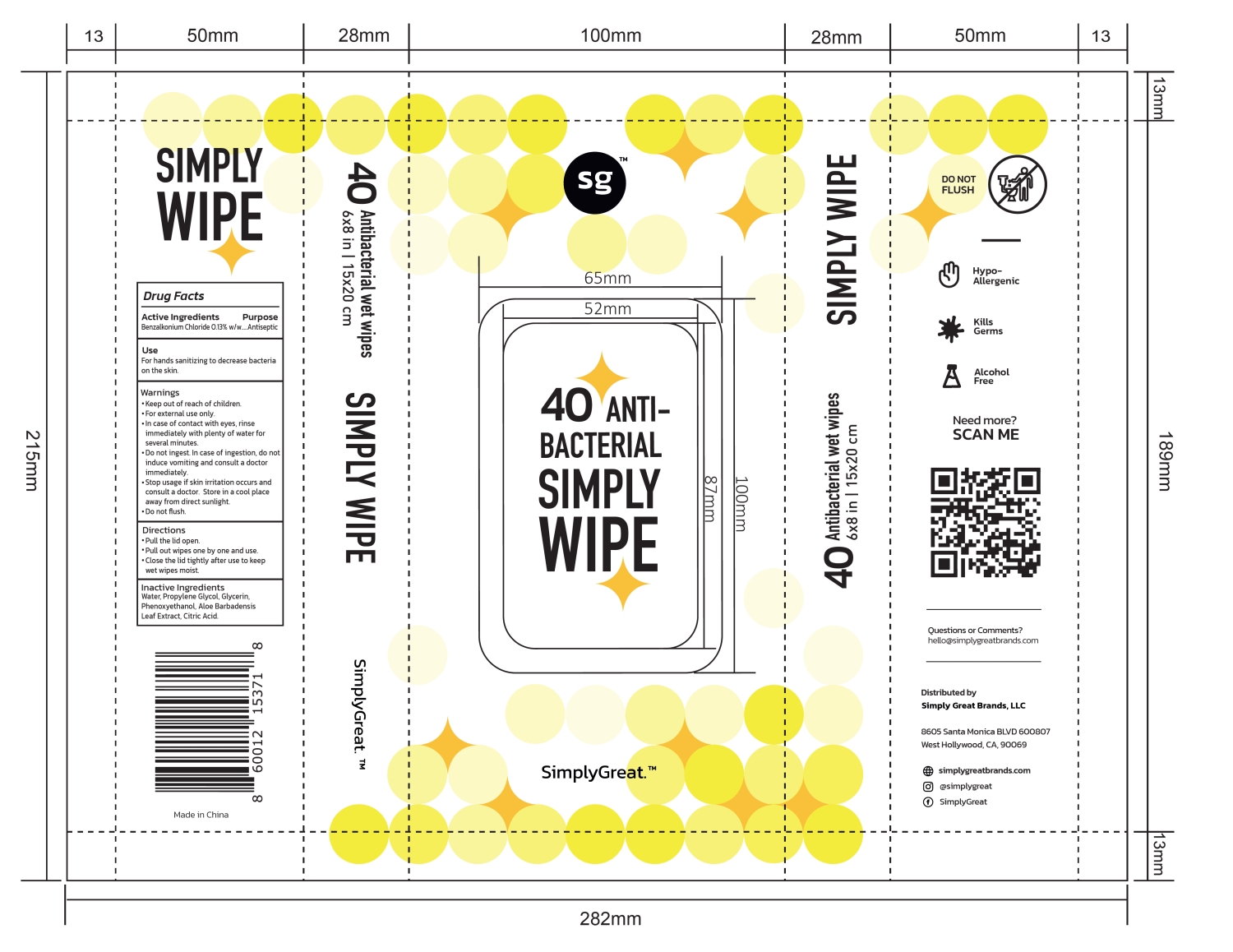 DRUG LABEL: SimplyGreat Antibacterial wet wipes
NDC: 85057-001 | Form: CLOTH
Manufacturer: Simply Great Brands LLC
Category: otc | Type: HUMAN OTC DRUG LABEL
Date: 20251223

ACTIVE INGREDIENTS: BENZALKONIUM CHLORIDE 0.13 g/100 g
INACTIVE INGREDIENTS: PROPYLENE GLYCOL; ALOE BARBADENSIS LEAF; GLYCERIN; CITRIC ACID; WATER; PHENOXYETHANOL

85057-001 SimplyGreat Antibacterial wet wipes

Active Ingredients

Benzalkonium Chloride 0.13% w/w

Purpose

Antiseptic

Use

For hands sanitizing to decrease bacteria on the skin.

Warnings

· Keep out of reach of children.

· For external use only.

· In case of contact with eyes, rinse immediately with plenty of water for several minutes.

· Do not ingest. In case of ingestion, do not induce vomiting and consult a doctor immediately.

· Stop usage if skin irritation occurs and consult a doctor. Store in a cool place away from direct sunlight.

· Do not flush.

· Keep out of reach of children.

Directions

· Pull the lid open.

· Pull out wipes one by one and use.

· Close the lid tightly after use to keep wet wipes moist.

Inactive Ingredients

Water, Propylene Glycol, Glycerin, Phenoxyethanol, Aloe Barbadensis Leaf Extract, Citric Acid.

PACKAGE LABEL

40 Antibacterial wet wipes
6×8 in | 15×20 cm
NDC: 85057-001-01